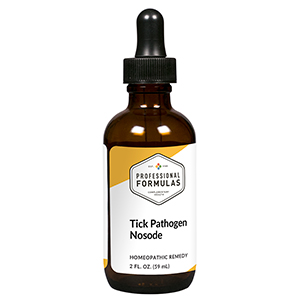 DRUG LABEL: Tick Pathogen Nosode
NDC: 63083-4030 | Form: LIQUID
Manufacturer: Professional Complementary Health Formulas
Category: homeopathic | Type: HUMAN OTC DRUG LABEL
Date: 20190815

ACTIVE INGREDIENTS: ANAPLASMA PHAGOCYTOPHILUM 30 [hp_X]/59 mL; BABESIA MICROTI 30 [hp_X]/59 mL; BARTONELLA HENSELAE 30 [hp_X]/59 mL; BORRELIA AFZELII 30 [hp_X]/59 mL; BORRELIA BURGDORFERI 30 [hp_X]/59 mL; VIOLA JAPONICA WHOLE 30 [hp_X]/59 mL; EHRLICHIA CHAFFEENSIS 30 [hp_X]/59 mL; HUMAN HERPESVIRUS 6 30 [hp_X]/59 mL; MYCOPLASMA PNEUMONIAE 30 [hp_X]/59 mL; COXIELLA BURNETII 30 [hp_X]/59 mL; RICKETTSIA RICKETTSII 30 [hp_X]/59 mL; FRANCISELLA TULARENSIS 30 [hp_X]/59 mL
INACTIVE INGREDIENTS: ALCOHOL; WATER

N30

ACTIVE INGREDIENTS

all the following at 30X, 60X:
Anaplasma phagocytophilum
Babesia microti
Bartonella henselae
Borrelia afzelii
Borrelia andersonii
Borrelia burgdorferi
Borrelia garinii
Borrelia japonica
Colorado tick fever
Ehrlichia chaffeensis
Herpes virus #6
Mycoplasma fermentans
Rickettsia burnetti
Rickettsia rickettsii
Tularemia

QUESTIONS

Professional Formulas

PO Box 2034 Lake Oswego, OR 97035

INDICATIONS

For the temporary relief of minor aches in the muscles or joints, chills, sweats, fatigue, occasional headache, or nausea.*

PURPOSE

*Claims based on traditional homeopathic practice, not accepted medical evidence. Not FDA evaluated.

WARNINGS

Persistent symptoms may be a sign of a serious condition. If symptoms persist or are accompanied by a fever, rash, or persistent headache, consult a doctor. Keep out of the reach of children. In case of overdose, get medical help or contact a poison control center right away. If pregnant or breastfeeding, ask a healthcare professional before use.

Keep out of the reach of children.

PREGNANCY OR BREAST FEEDING

If pregnant or breastfeeding, ask a healthcare professional before use.

DIRECTIONS

Place drops under tongue 30 minutes before/after meals. Adults and children 12 years and over: Take 10 to 15 drops once weekly or monthly. If mild symptoms are present, take 10 drops up to 3 times per day. Consult a physician for use in children under 12 years of age.

OTHER INFORMATION

Tamper resistant. If seal is broken, do not use. After opening, close container tightly and store at room temperature away from heat.

INACTIVE INGREDIENTS

20% ethanol, purified water.

LABEL

Est 1985

Professional Formulas

Complementary Health

Tick Pathogen Nosode

Homeopathic Remedy

2 FL. OZ. (59 mL)